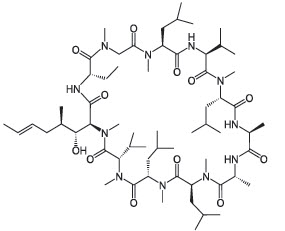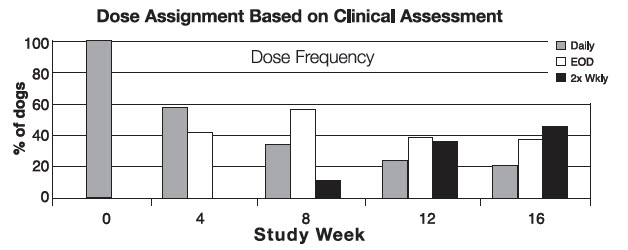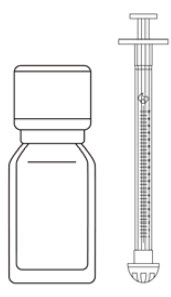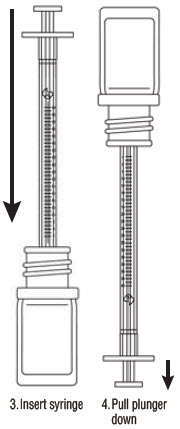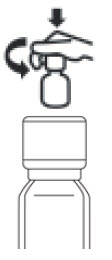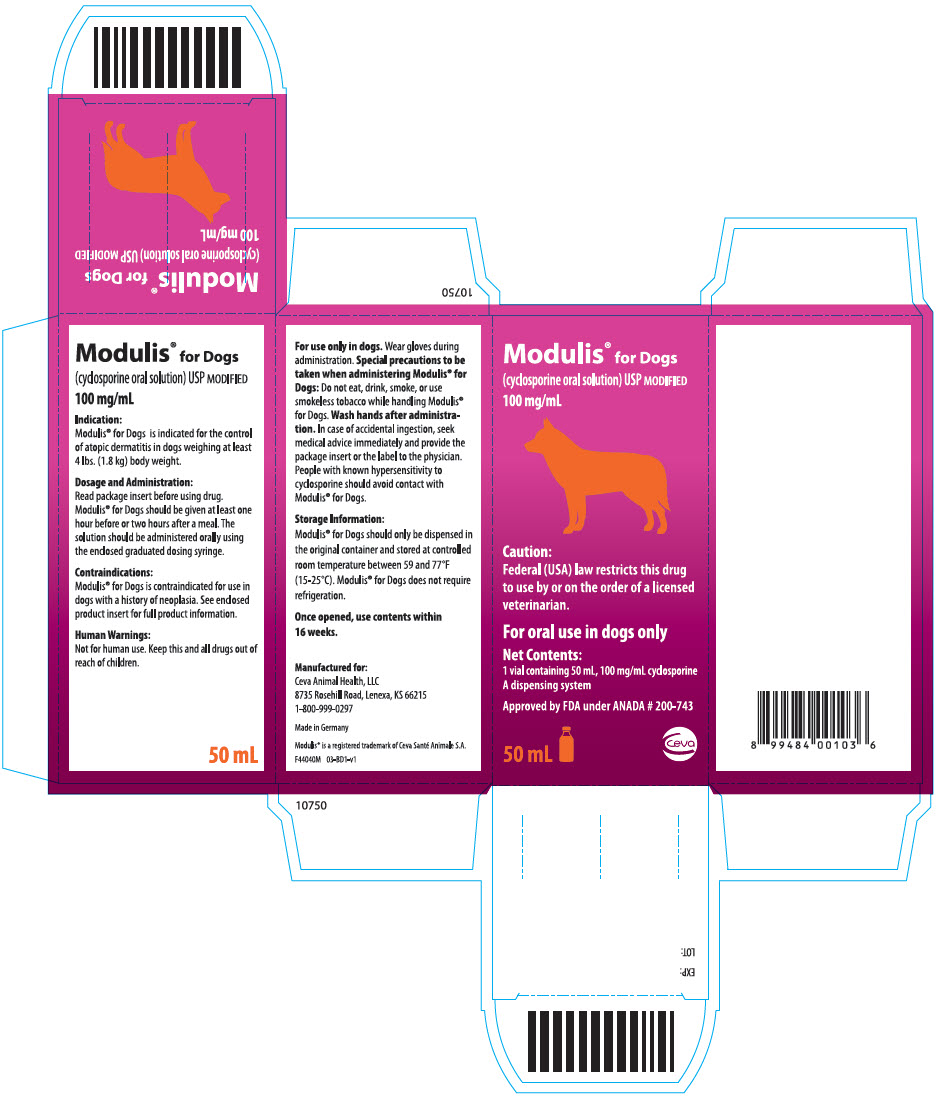 DRUG LABEL: Modulis for Dogs
NDC: 13744-535 | Form: SOLUTION
Manufacturer: Ceva Sante Animale
Category: animal | Type: PRESCRIPTION ANIMAL DRUG LABEL
Date: 20240805

ACTIVE INGREDIENTS: CYCLOSPORINE 100 mg/1 mL

Modulis® for Dogs
(cyclosporine oral solution) USP MODIFIED
100 mg/mL

Caution:

Federal (USA) law restricts this drug to use by or on the order of a licensed veterinarian. Keep this and all drugs out of reach of children.

Description:

MODULIS® for Dogs (cyclosporine oral solution) USP MODIFIED is an oral form of cyclosporine that immediately forms a microemulsion in an aqueous environment. Cyclosporine, the active ingredient in MODULIS® for Dogs, is a cyclic polypeptide, immune modulating agent consisting of 11 amino acids. It is produced as a metabolite by the fungal species Beauveria nivea.

Chemically, cyclosporine A is designated Cyclo[[(E)-(2S,3R,4R)-3-hydroxy-4-methyl-2-(methylamino)-6-octenoyl]-L-2-aminobutyryl-N-methylglycyl-N-methyl-L-leucyl-L-valyl-N-methyl-L-leucyl -L-alanyl-D-ananyl-N-methyl-L-leucyl-N-methyl-L-leucyl-N-methyl-L-valyl].

The structural formula is:

Indications:

MODULIS® for Dogs is indicated for the control of atopic dermatitis in dogs weighing at least 4 lbs. (1.8 kg) body weight.

Dosage and Administration:

Always provide the Instructions for Assembling the Dispensing System and Preparing a Dose of MODULIS® for Dogs and the Information for Dog Owners with prescription. The initial dose of MODULIS® for Dogs is 5 mg/kg/day as a single daily dose for 30 days. Following this initial daily treatment period, the dose of MODULIS® for Dogs may be tapered by decreasing the frequency of dosing to every other day or twice weekly, until a minimum frequency is reached which will maintain the desired therapeutic effect. MODULIS® for Dogs should be given at least one hour before or two hours after a meal. If a dose is missed, the next dose should be administered (without doubling) as soon as possible, but dosing should be no more frequent than once daily. The dispensing system includes oral dosing syringes to accompany MODULIS® for Dogs:

- For dogs 4 lbs to 40 lbs, use the 1 mL syringe: The 1 mL syringe is graduated in 1 pound (lb) increments. To dose the dog, the syringe should be filled to the nearest 1 lb graduation corresponding to the dog's body weight in lbs (round down to the nearest whole lb if 0.1 to 0.4 lb, or round up to the nearest whole lb if 0.5 to 0.9 lb). Each 1-lb graduation on the 1 mL syringe delivers a volume of 0.023 mL, providing 2.3 mg/lb (5 mg/kg) dose.

- For dogs 41 lbs to 125 lbs, use the 3 mL syringe: The 3 mL syringe is graduated in 5 pound (lb) increments. To dose the dog, the syringe should be filled to the nearest 5 lb graduation corresponding to the dog's body weight in lbs (round down to the nearest whole lb if 0.1 to 0.4 lb, or round up to the nearest whole lb if 0.5 to 0.9 lb). Each 5-lb graduation on the 3 mL syringe delivers a volume of 0.115 mL, providing 2.3 mg/lb (5 mg/kg) dose.

Do not rinse or clean the oral dosing syringe between uses.

Note: Always close the bottle with the child-resistant screw cap after each use.

The 1 mL syringe is graduated in 1 lb increments corresponding to 0.023 mL/lb. This syringe is for dosing dogs 4 to 40 lb. The 1 mL syringe will be included with the 4.7, 15, and 30 mL bottles.

The 3 mL syringe is graduated in 5 lb increments corresponding to 0.115 mL/5 lb. This syringe is for dosing dogs 41 to 125 lb. The 3 mL syringe will be included with the 30 and 50 mL bottles.

(See Instructions for Assembling the Dispensing System and Preparing a Dose of MODULIS® for Dogs)

Contraindications:

MODULIS® for Dogs is contraindicated for use in dogs with a history of neoplasia. Do not use in dogs with a hypersensitivity to cyclosporine.

Warnings:

MODULIS® for Dogs (cyclosporine oral solution) is a systemic immunosuppressant that may increase the susceptibility to infection and the development of neoplasia.

Human Warnings:

Not for human use. Keep this and all drugs out of reach of children.

For use only in dogs. Wear gloves during administration.

Special precautions to be taken when administering MODULIS® for Dogs: Do not eat, drink, smoke, or use smokeless tobacco while handling MODULIS® for Dogs.

Wash hands after administration.

In case of accidental ingestion, seek medical advice immediately and provide the package insert or the label to the physician.

People with known hypersensitivity to cyclosporine should avoid contact with MODULIS® for Dogs.

Precautions:

The safety and effectiveness of cyclosporine has not been established in dogs less than 6 months of age or less than 4 lbs body weight. MODULIS® for Dogs is not for use in breeding dogs, pregnant or lactating bitches.

As with any immunomodulation regimen, exacerbation of sub-clinical neoplastic and infectious conditions may occur.

Gastrointestinal problems and gingival hyperplasia may occur at the initial recommended dose. (See Animal Safety).

MODULIS® for Dogs may cause elevated levels of serum glucose and should be used with caution in cases with diabetes mellitus. If signs of diabetes mellitus develop following the use of MODULIS® for Dogs, consideration should be given to tapering or discontinuing the dose.

MODULIS® for Dogs should be used with caution with drugs that affect the P-450 enzyme system. Simultaneous administration of MODULIS® for Dogs with drugs that suppress the P-450 enzyme system, such as azoles (e.g. ketoconazole), may lead to increased plasma levels of cyclosporine. Since the effect of cyclosporine use on dogs with compromised renal function has not been studied, MODULIS® for Dogs should be used with caution in dogs with renal insufficiency.

There have been reports of convulsions in human adult and pediatric patients receiving cyclosporine, particularly in combination with high dose methylprednisolone. (See Animal Safety).

Killed vaccines are recommended for dogs receiving MODULIS® for Dogs because the impact of cyclosporine on the immune response to modified live vaccines is unknown. (See Animal Safety).

Adverse Reactions:

A total of 265 dogs were included in the field study safety analysis. One hundred and eleven (111) dogs were treated with placebo for the first 30 days. For the remainder of the study, all dogs received cyclosporine capsules.

Fourteen dogs withdrew from the study due to adverse reactions. Four dogs withdrew from the study after vomiting. One dog each withdrew from the study after diarrhea; vomiting, diarrhea and pruritus; vomiting, depression and lethargy; lethargy, anorexia and hepatitis; gingival hyperplasia, lethargy, polyuria/polydipsia and soft stool; seizure; sebaceous cyst; pruritus; erythema; or otitis externa.

Vomiting and diarrhea were the most common adverse reactions occurring during the study. In most cases, signs spontaneously resolved with continued dosing. In other cases, temporary dose modifications (brief interruption in dosing, divided dosing, or administration with a small amount of food) were employed to resolve signs.

Persistent otitis externa, urinary tract infections, anorexia, gingival hyperplasia, lymphadenopathy and lethargy were the next most frequent adverse events observed. Gingival hyperplasia regressed with dose tapering. Owners of four dogs reported seizures while dogs were receiving cyclosporine. In one dog, seizures were the result of a brain tumor diagnosed one month into the study. Another dog experienced seizures before and after the study.

Otitis externa, allergic otitis, or pinna erythema, with or without exudates, commonly accompanies atopy. Many dogs entered the study with otitis externa, which did not resolve without otic treatment. New cases of otitis externa, allergic otitis, or pinna erythema developed while dogs were receiving cyclosporine. However, the incidence rate was lower with cyclosporine compared to placebo. A change in the dose frequency was not necessary when new cases occurred.

Number of Dogs Displaying Each Clinical Observation in the Field Study
Clinical Sign | % out of 265
Vomiting | 30.9%
Diarrhea | 20.0%
Persistent Otitis Externa | 6.8%
Urinary Tract Infection | 3.8%
Anorexia | 3.0%
Lethargy | 2.3%
Gingival Hyperplasia | 2.3%
Lymphadenopathy | 2.3%

The following clinical signs were reported in less than 2% of dogs treated with cyclosporine in the field study: constipation, flatulence, Clostridial organisms in the feces, nausea, regurgitation, polyuria/polydipsia, strong urine odor, proteinuria, pruritus, erythema/flushed appearance, pyoderma, sebaceous adenitis, crusty dermatitis, excessive shedding, coarse coat, alopecia, papillomas, histiocytoma, granulomatous mass or lesion, cutaneous cyst, epulis, benign epithelial tumor, multiple hemangioma, raised nodule on pinna, seizure, shaking/trembling, hind limb twitch, panting, depression, irritability, hyperactivity, quieter, increased light sensitivity, reluctance to go outside, weight loss, hepatitis.

The following clinical signs were observed in 1.5-4.5% of dogs while receiving the placebo: vomiting, diarrhea and urinary tract infection. The following clinical signs were observed in less than 1% of dogs receiving the placebo: anorexia, otitis externa, cutaneous cysts, corneal opacity, lymphadenopathy, erythema/flushed appearance.

Clinical Pathology Changes: During the study, some dogs experienced changes in clinical chemistry parameters while receiving cyclosporine, as described in the following table:

Clinical Chemistry | % Affected (out of 265)
Elevated Creatinine | 7.8%
Hyperglobulinemia | 6.4%
Hyperphosphatemia | 5.3%
Hyperproteinemia | 3.4%
Hypercholesterolemia | 2.6%
Hypoalbuminemia | 2.3%
Hypocalcemia | 2.3%
Elevated BUN | 2.3%

In addition, the following changes in clinical chemistry parameters were noted in less than 2% of dogs: hypernatremia; hyperkalemia, elevated ALT, elevated ALP, hypercalcemia and hyperchloremia. These clinical pathology changes were generally not associated with clinical signs.

Post-approval Experience: (Rev 2014)

The following adverse events are based on post-approval adverse drug experience reporting. Not all adverse reactions are reported to FDA CVM.

It is not always possible to reliably estimate the adverse event frequency or establish a causal relationship to product exposure using this data. The following adverse events are grouped by body system and are presented in decreasing order of reporting frequency.

Gastrointestinal: Emesis, diarrhea, gingival hyperplasia, hemorrhagic diarrhea, abdominal pain, hematemesis, digestive tract hemorrhage, hypersalivation, retching, flatulence, tenesmus, intestinal stasis, digestive tract hypermotility, melena, pancreatitis, involuntary defecation

General: Lethargy, anorexia, weight loss, polydipsia, hyperthermia, pale mucous membrane, general pain, collapse, dehydration, edema

Dermatologic: Pruritus, dermatitis and eczema, alopecia, erythema, papilloma, bacterial skin infection, skin lesion, skin and/or appendage neoplasm, pigmentation disorder, hair change, hyperkeratosis, histiocytoma, fungal skin infection, dermal cyst(s), desquamation

Behavioral: Hyperactivity, behavioral changes, anxiety, vocalization, aggression, inappropriate urination, disorientation

Neurologic: Muscle tremor, convulsion, ataxia, paresis

Respiratory: Tachypnea, dyspnea, cough

Urologic: Polyuria, urine abnormalities (hematuria, urinary tract infection, proteinuria, glucosuria, decreased urine concentration) urinary incontinence, cystitis, renal failure, renal insufficiency

Immune: Urticaria, anaphylaxis, allergic edema

Blood and lymphatic: Lymphadenopathy, anemia, hypoalbuminemia, leukopenia

Hepatic: Elevated Liver Enzymes, hepatopathy, hepatomegaly, hepatitis

Musculoskeletal: Lameness, limb weakness, myositis

Ear and labyrinth: Otitis externa

Cardio-vascular: Tachycardia

Endocrine: Diabetes mellitus, hyperglycemia

In some cases, death/euthanasia has been reported as an outcome of the adverse events listed above.

Neoplasms have been reported in dogs taking cyclosporine, including reports of lymphoma/lymphosarcoma and mast cell tumor. It is unknown if these were preexisting or developed de novo while on cyclosporine.

Diabetes mellitus has been reported; West Highland White Terriers are the most frequently reported breed.

To report suspected adverse drug events, for technical assistance or to obtain a copy of the Safety Data sheet, contact Ceva Animal Health, LLC at 1-800-999-0297 or ceva.com.

For additional information about adverse drug experience reporting for animal drugs, contact FDA at 1-888-FDA-VETS or http://www.fda.gov/reportanimalae.

Clinical Pharmacology:

Cyclosporine is an immunosuppressive agent that has been shown to work via suppression of T-helper and T-suppressor cells and inhibition of interleukin-2.

It does not depress hematopoiesis or the function of phagocytic cells. A decrease in CD4 and CD8 cells was not seen in dogs receiving 20 mg/kg/day of cyclosporine for 56 days. MODULIS® for Dogs is not a corticosteroid or an antihistamine.

MECHANISM OF ACTION

Metabolism:

Cyclosporine is extensively metabolized by the cytochrome P-450 enzyme system in the liver, and to a lesser degree in the gastrointestinal tract and the kidney.

The metabolism of cyclosporine can be altered by the co-administration of a variety of agents (See Precautions).

Effectiveness Field Study:

A multisite, placebo controlled, double masked, field study was conducted in the United States and Canada using 16 investigators. Two hundred sixty five (265) dogs aged 1-10 years, weighing 4-121 lbs received either cyclosporine capsules at 5 mg/kg/day or placebo capsules. After 30 days, placebo dogs were switched to cyclosporine capsules.

Dogs were treated with cyclosporine capsules for a total of 4 months. No additional therapy with antihistamines, corticosteroids or medicated shampoos was permitted.

Evaluations for pruritus and for skin lesions to derive a Canine Atopic Dermatitis Extent and Severity Index (CADESI) score occurred at enrollment and at monthly intervals.

One hundred ninety-two (192) dogs were included in the statistical analysis of effectiveness.

At the end of the 30 day placebo controlled period, CADESI scores of dogs treated with cyclosporine capsules improved by 45% from enrollment, while CADESI scores of dogs treated with placebo worsened by 9%. Seventy-four percent (74%) of cyclosporine capsule treated dogs showed improvement in their pruritus scores over the first 30 day period, while only 24% of the placebo treated dogs showed an improvement. Owner and Veterinary Global Assessment in response to treatment also demonstrated statistically significant (p<0.0001) improvement. After 4 weeks of therapy, Owner and Veterinary Global Assessments showed approximately twice as much improvement in the cyclosporine capsule treated dogs as compared to placebo treated dogs.

Improvements in pruritus accompanied by 50% or 75% improvements in CADESI scores resulted in dose reductions to every other day or twice weekly respectively. Not all dogs were able to decrease to twice weekly dosing. Some animals required upward or downward dosage adjustments during the study. Such adjustments should be expected during therapy of this disease. Dogs unable to decrease from once daily dosing after 60 days were considered dose reduction failures for the purposes of the study.

The results of dose assignments, based on the study criteria, for each 4-week dosing period, are shown in the graph.

Analysis of blood levels of cyclosporine drawn during the study demonstrated no correlation between blood cyclosporine levels and CADESI scores or pruritus; therefore monitoring blood cyclosporine levels is not an appropriate predictor of effectiveness.

Animal Safety:

In a 52-week oral study with dose levels of 0, 1, 3, and 9 times the target initial daily dose, emesis, diarrhea and weight loss were seen in all cyclosporine treated groups with increasing frequency as the dose increased.

Multilocular papilloma-like lesions of the skin were observed in 5 out of 8 high dose animals between weeks 20 and 40. These changes regressed spontaneously after drug was withdrawn.

Other findings in the mid and high dose animals included swollen gums due to chronic gingivitis and periodontitis, lower serum albumin and higher cholesterol, triglyceride, IgA and IgG. Hematological findings consisted of anemia and decreased leukocyte counts in a few high dose animals. Erythrocyte sedimentation rates were increased at all dose levels in a dose dependent fashion. Notable histopathological findings were limited to lymphoid atrophy, hypertrophic gums (from gingivitis) and slight regenerative changes of the renal tubular epithelium in high dose animals. The findings were shown to be reversible during a 12-week recovery phase of the study.

In a 90-day study with cyclosporine, dogs were dosed in one of two patterns: either 1, 3, or 5× the maximum recommended target initial daily dose for 90 days, or 1, 3, or 5× the maximum recommended target initial daily dose for 30 days followed by tapering to mimic the recommended clinical dosing pattern. The maximum recommended dose, when administered for 90 days causes callus-like lesions on the footpads, red/swollen pinnae, mild to moderate gingival proliferation, hyperkeratotic areas on the integument, hair loss, salivation, vomiting, and diarrhea/abnormal stools. These clinical signs lessened in severity or resolved as the drug was tapered to a lower dose. Increased erythrocyte sedimentation rate, hyperproteinemia, hyperglobulinemia, hypoalbuminemia, hypocalcemia, hypophosphatemia, and hypomagnesemia were observed at three and five times the maximum recommended dose. These resolved as the dose was tapered.

When administered at higher than the maximum recommended dose, raised skin lesions, papilloma-like areas on the integument, popliteal lymph node enlargement, and weight loss were also seen. There were no cyclosporine related changes in urinalysis, ECG, blood pressure, or ophthalmologic exams.

Gross necropsy revealed epithelial changes consistent with those seen on physical examination. Proliferation of gingiva and toe pad epithelium was seen in all cyclosporine dosed groups, and was seen in a dose dependent fashion. The degree of the proliferation was greater in dogs in the non-tapered groups as compared to the tapered groups.

Similar changes were noted on histopathologic examination of the cutaneous changes seen on physical examination. These lesions were characterized by epidermal hyperplasia, chronic dermatitis and hyperkeratosis.

Methylprednisolone combination: Twenty-four dogs were administered 1 mg/kg/day methylprednisolone alone for 14 days followed by 20 mg/kg/day cyclosporine either alone or in combination with methylprednisolone, or placebo for 14 days. There was no evidence of seizures/convulsions or neurological signs.

Vaccination effect: The effect of cyclosporine administration on the immunological response to vaccination was evaluated in a study in which 16 dogs were dosed with either cyclosporine at 20 mg/kg/day (4× the initial daily dose) or placebo for 56 days. All dogs were vaccinated on Day 27 with a killed commercial rabies virus and a multivalent vaccine (DHLPP) which included a modified live virus.

Antibody titers for rabies, canine distemper, canine adenovirus type 2, parainfluenza, parvovirus, Leptospira canicola, and Leptospira icterohaemmorrhagiae were examined on Days 0, 27 (prior to vaccination), 42 and 56. Quantification of CD4, CD8, and CD3 T-lymphocytes was analyzed.

Clinical changes included soft stool and dermatologic changes consistent with those seen in previous studies. Antibody titers did not rise in dogs treated with cyclosporine or the placebo for any component of the multivalent vaccine which included a modified live virus while all animals demonstrated a significant increase in antibody rabies titer by Day 42 or 15 days post-revaccination. No effect was seen on T-lymphocytes.

Storage Conditions:

MODULIS® for Dogs should only be dispensed in the original container and stored at controlled room temperature between 59 and 77°F (15-25°C). Modulis® for Dogs does not require refrigeration. Once opened, use contents within 9 weeks for the 4.7 mL container and 16 weeks for the 15, 30, and 50 mL containers.

How Supplied:

MODULIS® for Dogs is supplied in glass amber bottles of 4.7, 15, 30, and 50 mL at 100 mg/mL.

A dispensing system is included (See Instructions for Assembling the Dispensing System and Preparing a Dose of MODULIS® for Dogs).

Manufactured for:
Ceva Animal Health, LLC.
Lenexa, KS 66215

Approved by FDA under ANADA # 200-743
MODULIS® is a registered trademark of Ceva Santé Animale S.A.
REV:10/23
F44020Q 08-A1-v1

Made in Germany

PATIENT INFORMATION

Instructions for Assembling the Dispensing System and Preparing a Dose of MODULIS® for Dogs (cyclosporine oral solution) USP MODIFIED.

Assembling the Dispensing System

The dispensing system consists of 2 parts:

1. A bottle containing the medicine, fitted with a pre-inserted plastic adapter and a screw cap to close the bottle after use. Do not remove the adapter from the neck of the bottle. It must remain in place for the duration of use.
2. An oral dosing syringe that fits into the top of the plastic adapter to withdraw the prescribed dose of the medicine from the bottle. The oral dosing syringe comes with a plastic cap. Save the plastic cap to protect the oral dosing syringe during storage between each use.

Note: To prepare a dose, carefully follow the instructions for Preparing a Dose of Medicine.

Preparing a Dose of Medicine.

1. Push and turn the child-resistant screw cap to open the bottle. Note: Always close the bottle with the child-resistant screw cap after use.
2. Remove the plastic cap and check that the plunger of the oral dosing syringe is pushed all the way down.
3. Keep the bottle upright and insert the oral dosing syringe firmly into the plastic adapter.
4. Invert the bottle/syringe, and slowly pull the plunger down so that the oral dosing syringe fills with the medicine.
5. Expel any large bubbles by pushing and pulling the plunger a few times. The presence of a few tiny bubbles is not important for dose accuracy.
6. Withdraw the dose of medicine prescribed by your veterinarian. The scale on the oral dosing syringe corresponds to the dog's body weight.

Note: If the prescribed dose is more than the maximum volume marked on the oral dosing syringe, you will need to reload the syringe to withdraw the full dose.

7. Return the bottle/syringe to the upright position, and gently remove the oral dosing syringe from the plastic adapter.

You can now place the oral dosing syringe over a small amount of food or introduce the syringe in the mouth of your dog and push the medicine out of the syringe.

See Information for Dog Owners for complete administration instructions.

Do not rinse or clean the oral dosing syringe between uses. Replace the plastic cap to store the oral dosing syringe between each use.

MODULIS® for Dogs should only be dispensed in the original container and stored between 59 and 77°F (15 - 25°C). MODULIS® for Dogs does not require refrigeration. Once opened, use contents within 9 weeks for the 4.7 mL container and 16 weeks for the 15, 30, and 50 mL containers.
Keep out of reach of children
Always close the bottle with the child-resistant screw cap after use. To provide a child-resistant closure, push down on the child-resistant screw cap as you turn it.

MODULIS® for DOGS (cyclosporine oral solution)
USP MODIFIED

Information for Dog Owners

MODULIS® for Dogs is indicated for the control of atopic dermatitis in dogs weighing at least 4 lbs. (1.8 kg) body weight. Dogs with atopic dermatitis scratch, lick and chew their skin which can cause red, raised crusty bumps, open sores and/or hair loss.

Atopic dermatitis is a common skin disease in dogs and is caused by allergens such as house dust mites or pollens which stimulate an exaggerated immune response. The disease is chronic, recurrent, and requires lifelong management.

This summary contains important information about MODULIS® for Dogs. You should read this information before starting your dog on MODULIS® for Dogs. This sheet is provided only as a summary and does not take the place of instructions from your veterinarian. Talk to your veterinarian if you do not understand any of this information or you want to know more about MODULIS® for Dogs.

What is MODULIS® for Dogs?

MODULIS® for Dogs is an oral solution of cyclosporine that lowers the immune response. MODULIS® for Dogs selectively acts on the immune cells involved in the allergic reaction. MODULIS® for Dogs reduces the inflammation and itching associated with atopic dermatitis.

What kind of results can I expect when my dog takes MODULIS® for Dogs for the control of atopic dermatitis?

MODULIS® for Dogs should be given daily until improvement is seen. This will generally be the case within 30 days. You should contact your veterinarian if you are not satisfied with your dog's response. Once the signs of atopic dermatitis are satisfactorily controlled, your veterinarian may reduce the frequency of administration of the product. Dose adjustment should only be carried out in consultation with your veterinarian. Your veterinarian will perform a clinical assessment at regular intervals and adjust the frequency of administration up or down according to the clinical response obtained.

What dogs should not take MODULIS® for Dogs?

Your dog should not be given MODULIS® for Dogs if s/he:

- Has a history of cancer or may possibly have cancer
- Has a history of seizures, diabetes mellitus, and infections
- Is hypersensitive to cyclosporine

What to discuss with your veterinarian before giving MODULIS® for Dogs to your dog.

Tell your veterinarian about:

- Any digestive upset (vomiting or diarrhea) your dog has had
- Any history of lack of appetite and/or weight loss your dog has had
- Any serious disease or health conditions your dog has had
- Any allergies that your dog has now or has had
- All medications that you are giving your dog or plan to give your dog, including those you can get without prescription (over the counter) and any dietary supplements
- If you plan to breed your dog, or if your dog is pregnant or nursing

Talk to your veterinarian about:

- What tests might be done before MODULIS® for Dogs is prescribed
- The potential side effects your dog may experience while taking MODULIS® for Dogs
- How often your dog may need to be examined by your veterinarian
- The risks and benefits of using MODULIS® for Dogs

What are the possible side effects that may occur in my dog during therapy with MODULIS® for Dogs?

MODULIS® for Dogs, like all other drugs, may cause some side effects in individual dogs. These are normally mild, but serious side effects have been reported in dogs taking MODULIS® for Dogs. Serious side effects can, in rare situations, result in death. It is important to stop the medication and contact your veterinarian immediately if you think your dog may have a medical problem or side effect while on MODULIS® for Dogs.

To report adverse effects, access medical information, or obtain additional product information call 1-800-999-0297. In clinical studies, the most commonly reported side effect for cyclosporine was vomiting and diarrhea. In most cases, the vomiting and diarrhea stopped with continued use or dose modification. Persistent otitis externa, urinary tract infection, anorexia, lethargy, gingival hyperplasia, and lymphadenopathy were the next most frequent side effects observed. Persistent, progressive weight loss may be associated with more serious side effects. You should monitor your dog's appetite and body weight. If you think that your dog is losing weight, you should contact your veterinarian. MODULIS® for Dogs may increase susceptibility to infection and to the development of tumors.

MODULIS® for Dogs should only be given to dogs.

People should not take MODULIS® for Dogs. Keep MODULIS® for Dogs and all medication out of reach of children. Call your physician immediately if you accidentally swallow MODULIS® for Dogs.

How to give MODULIS® for Dogs to your dog.

MODULIS® for Dogs should be given according to your veterinarian's instructions. Your veterinarian will tell you what amount of MODULIS® for Dogs is right for your dog. MODULIS® for Dogs should be given at least one hour before or two hours after a meal. Do not change the way you give MODULIS® for Dogs to your dog without first speaking with your veterinarian. If a dose is missed, the next dose should be administered (without doubling) as soon as possible, but dosing should be no more frequent than once daily. Do not rinse or clean the oral dosing syringe between uses.

Advice on Correct Administration.

See Instructions for Assembling the Dispensing System and Preparing a Dose of MODULIS® for Dogs. If your veterinarian has already assembled the dispensing system, skip the instructions for assembling the dispensing system and follow the instructions for preparing a dose of medicine.

How to Store MODULIS® for Dogs.

MODULIS® for Dogs should be stored and dispensed in the original container at temperatures between 59 and 77°F (15-25°C).
MODULIS® for Dogs does not require refrigeration. Once opened, use contents within 9 weeks for the 4.7 mL container and 16 weeks for the 15, 30, and 50 mL containers.

Special precautions to be taken when administering MODULIS® for Dogs: Do not eat, drink, smoke, or use smokeless tobacco while handling MODULIS® for Dogs. Wear gloves during administration. Wash hands after administration. In case of accidental ingestion, seek medical advice immediately and show the package insert or the label to the physician. People with known hypersensitivity to cyclosporine should avoid contact with MODULIS® for Dogs.

Can MODULIS® for Dogs be given with other medications?

MODULIS® for Dogs should not be given with other drugs that may lower the immune response. Cyclosporine has been safely used in conjunction with other common medications. However, interactions with certain medications are possible. Therefore, always tell your veterinarian about all medications that you have given your dog in the past and all medications that you are planning to give with MODULIS® for Dogs.

What can I do in case my dog gets more than the prescribed amount of MODULIS® for Dogs?

Contact your veterinarian immediately if your dog gets more than the prescribed amount of MODULIS® for Dogs.

What else should I know about MODULIS® for Dogs?

If your dog becomes seriously ill, consult your veterinarian who will recommend the appropriate treatment.

This sheet provides a summary of information about MODULIS® for Dogs. If you have any questions or concerns about MODULIS® for Dogs or atopic dermatitis in dogs, talk to your veterinarian.

As with all prescribed medications, MODULIS® for Dogs should only be given to the dog for which it was prescribed. It should be given to your dog only for the condition for which it was prescribed, at the prescribed dose, and as directed by your veterinarian.

PRINCIPAL DISPLAY PANEL - 50 mL Bottle Carton

Modulis® for Dogs
(cyclosporine oral solution) USP MODIFIED
100 mg/mL

Caution:
Federal (USA) law restricts this drug
to use by or on the order of a licensed
veterinarian.

For oral use in dogs only

Net Contents:
1 vial containing 50 mL, 100 mg/mL cyclosporine
A dispensing system

Approved by FDA under ANADA # 200-743

50 mL

ceva